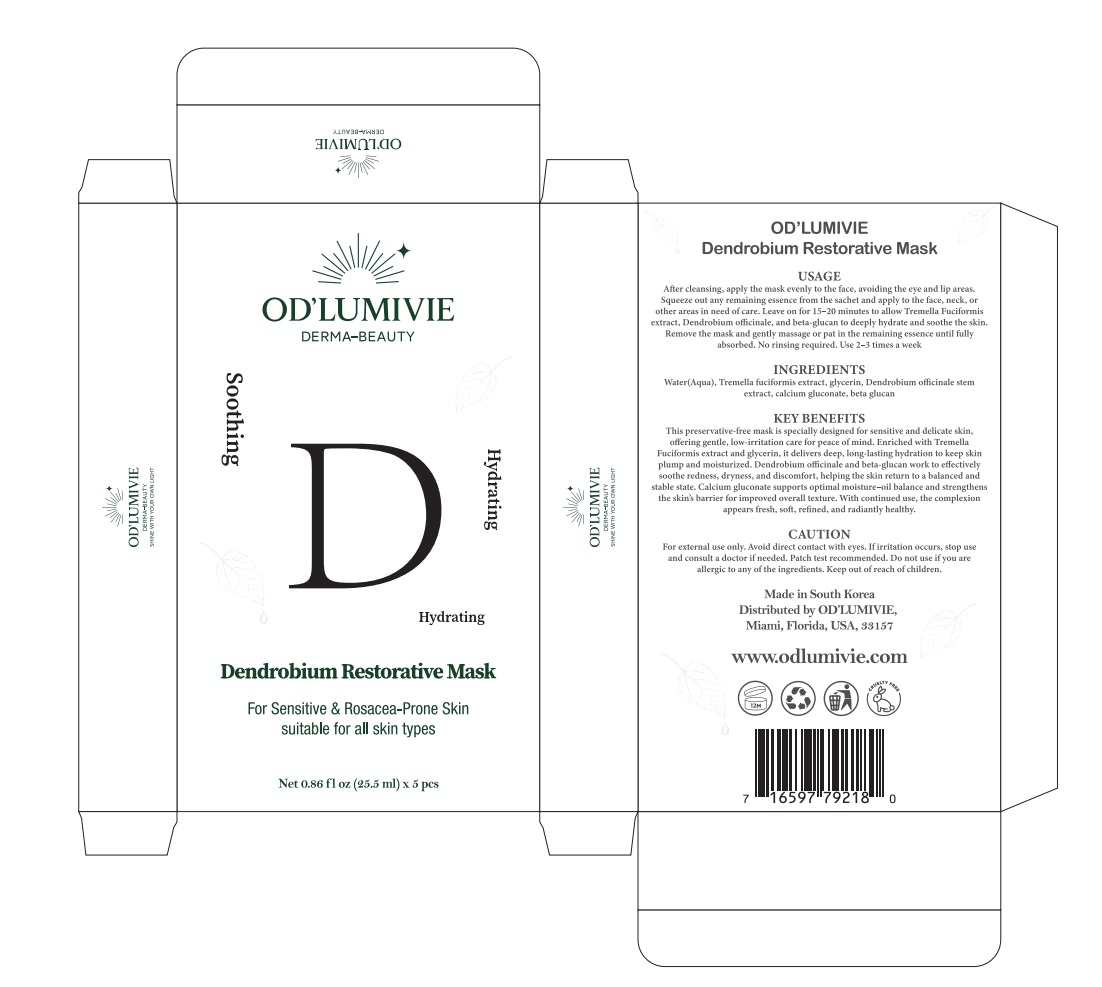 DRUG LABEL: ODLUMIVIE Dendrobium Restorative Mask
NDC: 87036-030 | Form: LIQUID
Manufacturer: OD’LUMIVIE
Category: otc | Type: HUMAN OTC DRUG LABEL
Date: 20251111

ACTIVE INGREDIENTS: DENDROBIUM OFFICINALE STEM 1 g/100 mL
INACTIVE INGREDIENTS: WATER; TREMELLA FUCIFORMIS WHOLE; GLYCERIN; CALCIUM GLUCONATE

ACTIVE INGREDIENT

INACTIVE INGREDIENT

Water(Aqua), Tremella fuciformis extract, glycerin, Dendrobium ofcinale stemextract, calcium gluconate, beta glucan

PURPOSE

KEY BENEFITS
This preservative-free mask is specially designed for sensitive and delicate skin,offering gentle, low-irritation care for peace of mind, Enriched with TremellaFuciformis extract and glycerin, it delivers deep, long-lasting hydration to keep skinplump and moisturized, Dendrobium ofcinale and beta-glucan work to effectivelysoothe redness, dryness, and discomfort, helping the skin return to a balanced andstable state. Calcium gluconate supports optimal moisture-oil balance and strengthensthe skin's barrier for improved overall texture. With continued use, the complexionappears fresh, soft, refned, and radiantly healthy.

WARNINGS

CAUTION
For external use only, Avoid direct contact with eyes. Ifirritation occurs, stop useand consult a doctor if needed. Patch test recommended, Do not use if you areallergic to any of the ingredients. Keep out of reach of children.

DO NOT USE

CAUTION
For external use only, Avoid direct contact with eyes. Ifirritation occurs, stop useand consult a doctor if needed. Patch test recommended, Do not use if you areallergic to any of the ingredients. Keep out of reach of children.

KEEP OUT OF REACH OF CHILDREN

CAUTION
For external use only, Avoid direct contact with eyes. Ifirritation occurs, stop useand consult a doctor if needed. Patch test recommended, Do not use if you areallergic to any of the ingredients. Keep out of reach of children.

STOP USE

CAUTION
For external use only, Avoid direct contact with eyes. Ifirritation occurs, stop useand consult a doctor if needed. Patch test recommended, Do not use if you areallergic to any of the ingredients. Keep out of reach of children.

USAGE
After cleansing, apply the mask evenly to the face, avoiding the eye and lip areas.Squeeze out any remaining essence from the sachet and apply to the face, neck, orother areas in need of care. Leave on for 15-20 minutes to allow Tremella Fuciformisextract, Dendrobium ofcinale, and beta-glucan to deeply hydrate and soothe the skin.Remove the mask and gently massage or pat in the remaining essence until fullyabsorbed. No rinsing required. Use 2-3 times a week

WHEN USING

USAGE
After cleansing, apply the mask evenly to the face, avoiding the eye and lip areas.Squeeze out any remaining essence from the sachet and apply to the face, neck, orother areas in need of care. Leave on for 15-20 minutes to allow Tremella Fuciformisextract, Dendrobium ofcinale, and beta-glucan to deeply hydrate and soothe the skin.Remove the mask and gently massage or pat in the remaining essence until fullyabsorbed. No rinsing required. Use 2-3 times a week

DOSAGE AND ADMINISTRATION

USAGE
After cleansing, apply the mask evenly to the face, avoiding the eye and lip areas.Squeeze out any remaining essence from the sachet and apply to the face, neck, orother areas in need of care. Leave on for 15-20 minutes to allow Tremella Fuciformisextract, Dendrobium ofcinale, and beta-glucan to deeply hydrate and soothe the skin.Remove the mask and gently massage or pat in the remaining essence until fullyabsorbed. No rinsing required. Use 2-3 times a week

PACKAGE LABEL

OD'LUMIVIEDendrobium Restorative Mask
OD'LUMIVIE
DERMA-BEAUTY
Soothing
Hydrating
Hydrating
Dendrobium Restorative Mask
IIAIWATGO
USAGEAfter cleansing, apply the mask evenly to the face, avoiding the eye and lip areas.Squeeze out any remaining essence from the sachet and apply to the face, neck, orother areas in need ofcare. Leave on for 15-20 minutes to allow Tremella Fuciformisextract, Dendrobium ofcinale, and beta-glucan to deeply hydrate and soothe the skinRemove the mask and gently massage or pat in the remaining essence until fullyabsorbed, No rinsing required, Use 2-3 times a week
INGREDIENTSWater(Aqua), Tremella fuciformis extract, glycerin, Dendrobium ofcinale stemextract,calcium gluconate, beta glucan
KEY BENEFITS
This preservative-free mask is specially desiened for sensitive and delicate skinofering gentle, low-irritation care for peace of mind. Enriched with TremellaFuciformis extract and glycerin, it delivers deep, long-lasting hydration to keep skirplump and moisturized, Dendrobium oficinale and beta-glucan work to efectivelysoothe redness, dryness, and discomfort, helping the skin return to a balanced andstable state, Calcium gluconate supports optimal moisture-oil balance and strengthenthe skin's barrier for improved overall texture, With continued use, the complexionappears fresh, soft, refned, and radiantly healthy,.
CAUTIONFor external use only, Avoid direct contact with eyes, lfirritation occurs, stop useand consult a doctor ifneeded, Patch test recommended, Do not use ifyou areallergic to any ofthe ingredients, Keep out ofreach of children.
Made in South KoreaDistributed by OD'LUMIVIEMiami, Florida.USA.33157
wwwodlumive.com
For Sensitive & Rosacea-Prone Skinsuitable for all skin types
Net 0.86 fl oz (25.5 ml)x 5 pcs